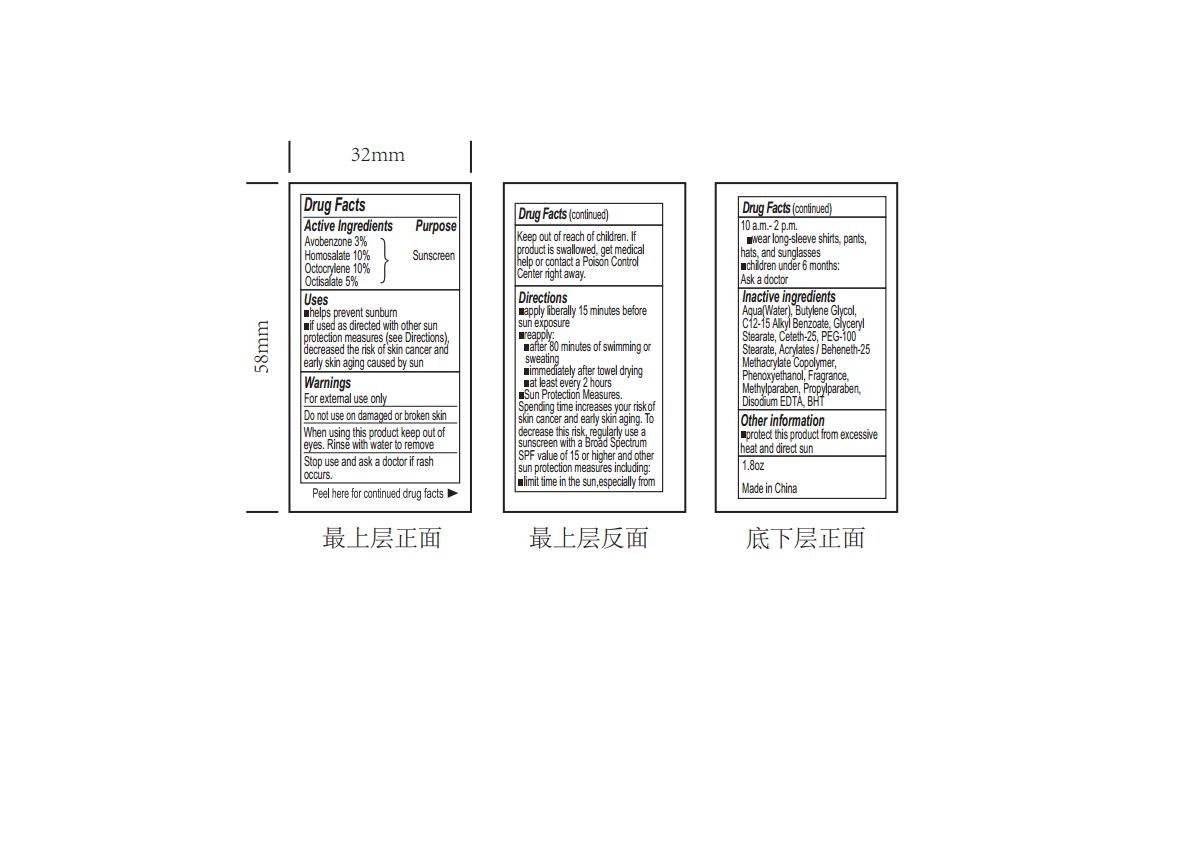 DRUG LABEL: SUNSCREEN
NDC: 82953-025 | Form: SPRAY
Manufacturer: Cosmuses Cosmetics (Ningbo) Co., Ltd.
Category: otc | Type: HUMAN OTC DRUG LABEL
Date: 20240921

ACTIVE INGREDIENTS: OCTOCRYLENE 10 g/100 mL; HOMOSALATE 10 g/100 mL; AVOBENZONE 3 g/100 mL; OCTISALATE 5 g/100 mL
INACTIVE INGREDIENTS: PEG-100 STEARATE; EDETATE DISODIUM; WATER; PHENOXYETHANOL; CETETH-25; METHYLPARABEN; GLYCERYL STEARATE SE; PROPYLPARABEN; BUTYLATED HYDROXYTOLUENE; FRAGRANCE 13576; ALKYL (C12-15) BENZOATE; BEHENETH-25 METHACRYLATE; BUTYLENE GLYCOL

sunscreen spray SPF30 (update 240921)

Drug Facts

Active ingredients

Avobenzone 3%

Homosalate 10%

Octocrylene 10%

Octisalate 5%

Purpose

Sunscreen

Uses

- Helps prevent sunburn
- If used as directed with other sun protection measures (see Directions), decreased the risk of skin cancer and early skin aging caused by sun.

Warnings

For external use only

Do not use on damaged or broken skin.

When using this product keep out of eyes. Rinse with water to remove.

Stop use and ask a doctor if rash occurs.

Keep out of reach of children. If prduct is swallowed, get medical help or contact a Poison Control Center right away.

Directions

- apply liberally 15minutes before sun exposure
- reapply:
- after 80 minutes of swimming or sweating
- immediate after towel drying
- at least every 2 hours
- Sun Protection Measures

Spending time increases your risk of skin cancer and early skin aging. To decreases this risk, regularly use a sunscreen with a Broad Spectrum SPF value of 15 or higher and other sun protection measures including:

- limit time in the sun, especially from 10a.m.- 2p.m.
- wear long-sleeve shirts, pants, hats and sunglasses
- children under 6 months

Ask a doctor

Inactive ingredients

Aqua, Butylene Glycol, C12-15 alkyl Benzoate, Glyceryl Stearate, Ceteth-25, PEG-100 stearate, Acrylates/ Beheneth-25 Methacrylate copolymer, Phenoxyethanol, Fragrance, Methylparaben, Propylparaben, Disodium EDTA, BHT.

Other information

Protect this product from excessive heat and direct sun